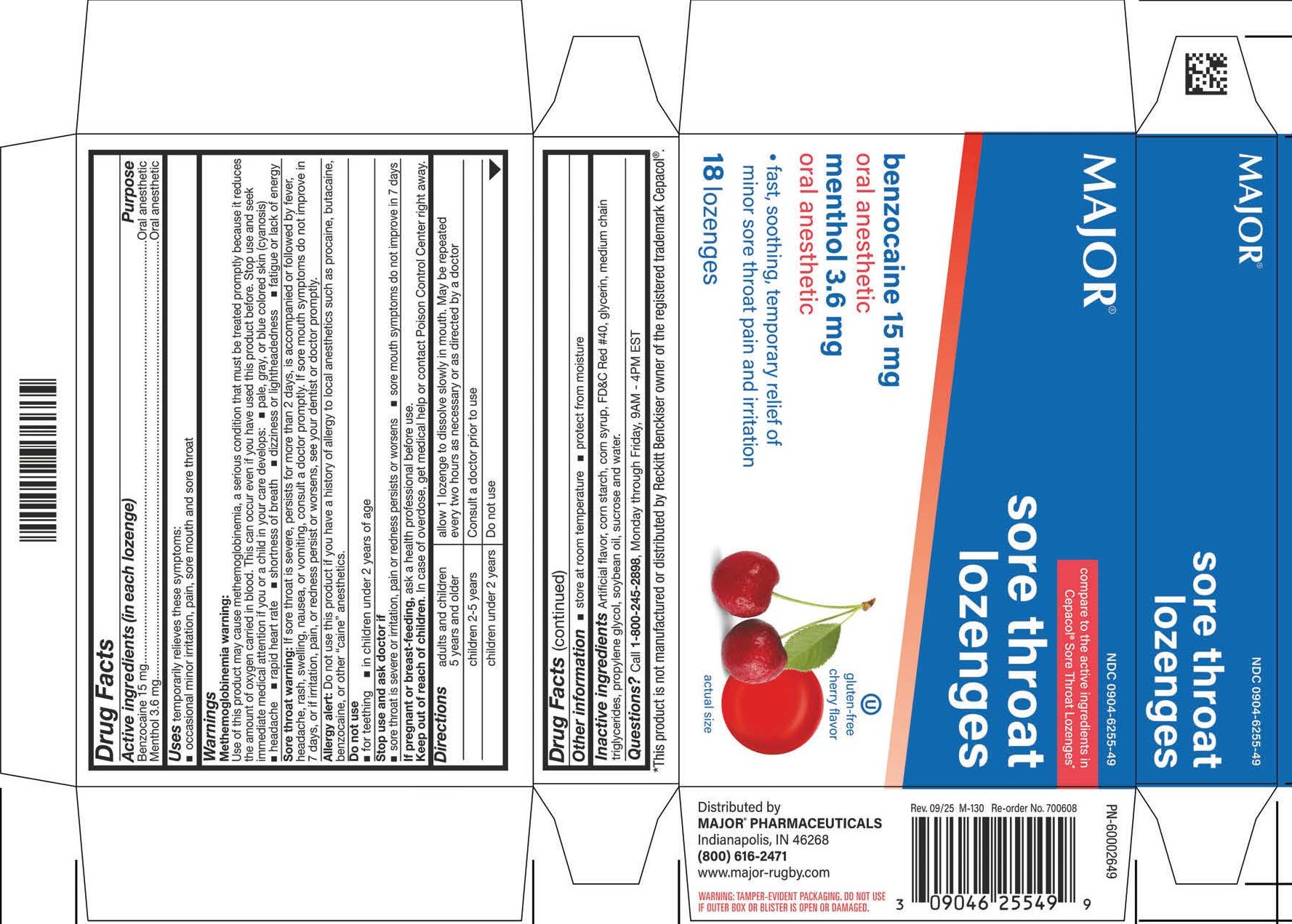 DRUG LABEL: Sore Throat Logenzes
NDC: 0904-6255 | Form: LOZENGE
Manufacturer: Major Pharmaceuticals
Category: otc | Type: HUMAN OTC DRUG LABEL
Date: 20260224

ACTIVE INGREDIENTS: BENZOCAINE 15 mg/1 1; MENTHOL 3.6 mg/1 1
INACTIVE INGREDIENTS: FD&C RED NO. 40; PROPYLENE GLYCOL; WATER; CORN SYRUP; ALLYL SUCROSE; HYDROGENATED SOYBEAN OIL

Cēpacol®
SORE THROAT

Drug Facts

ACTIVE INGREDIENT

Active ingredients (in each lozenge) | Purpose
Benzocaine 15 mg | Oral pain reliever
Menthol 3.6 mg | Oral pain reliever

Uses

temporary relief of occasional

- sore throat
- sore mouth
- minor mouth irritation
- pain associated with canker sores

Warnings

Allergy alert

- Do not use this product if you have a history of allergy to local anesthetics such as procaine, butacaine, benzocaine or any other 'caine' anesthetics.

Sore throat warning

- If sore throat is severe, persists for more than 2 days, is accompanied or followed by fever, headache, rash, nausea or vomiting consult a doctor promptly.

DO NOT USE

Do not usein a child under 5 years of age.

Stop use and ask a doctor or dentist if

- sore mouth symptoms do not improve in 7 days
- irritation, pain or redness persists or worsens
- swelling, rash or fever develops

PREGNANCY OR BREAST FEEDING

If pregnant or breast-feeding,ask a health professional before use.

KEEP OUT OF REACH OF CHILDREN

Keep this and all drugs out of the reach of children.

In case of overdose, get medical help or contact a Poison Control Center right away.

WHEN USING

Do not exceed recommended dosage.

Directions

- adults and children 5 years or older: allow lozenge to dissolve slowly in the mouth; may be repeated every 2 hours as needed or as directed by a doctor or dentist.
- children under 5 years of age: ask a doctor

Other information

- tamper evident packaging: Do not use if outer box or blister is open or damaged.
- store at room temperature
- protect contents from moisture

Inactive ingredients

Glucose syrup, N&A flavoring, propylene glycol, red #40, sucrose, and water. Soybean oil used as processing aid.

Questions?

Call 1-800-616-2471

Dist. by:
Major Pharmaceuticals
Livonia, MI 48150 USA